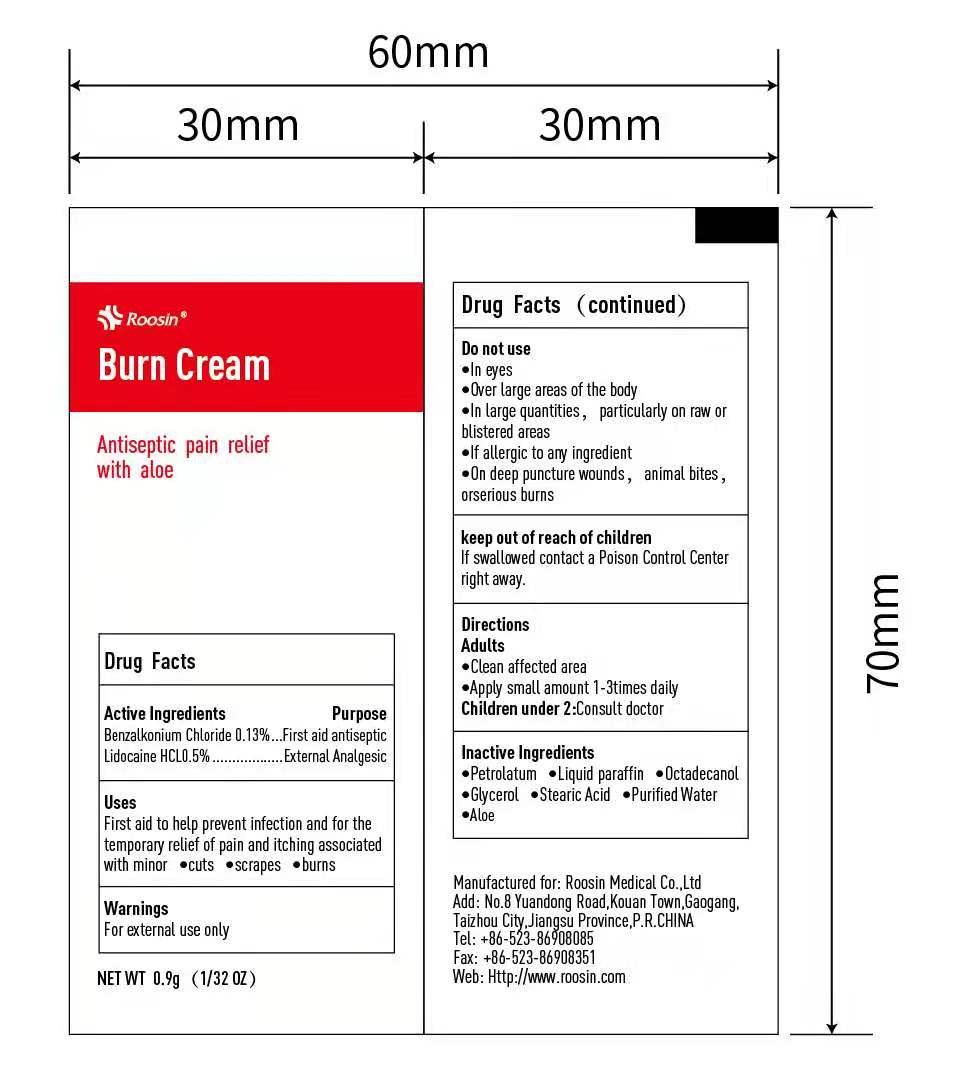 DRUG LABEL: Roosin Burn
NDC: 81552-002 | Form: CREAM
Manufacturer: ROOSIN MEDICAL CO., LTD
Category: otc | Type: HUMAN OTC DRUG LABEL
Date: 20211215

ACTIVE INGREDIENTS: LIDOCAINE HYDROCHLORIDE 0.5 g/100 g; BENZALKONIUM CHLORIDE 0.13 g/100 g
INACTIVE INGREDIENTS: ALOE; PETROLATUM; PARAFFIN; OCTADECANOL (MIXTURE OF ISOMERS); WATER; STEARIC ACID; GLYCEROL FORMAL

81552-002 Burn Cream

Active Ingredient

Banzalkonium Chloride 0.13%

Lidocaine Chloride 0.5%

Purpose

First Aid Antiseptic

External Analgesic

Antiseptic and antipyrotic

Use

First aid to help prevent infection and for temporary relief of pain and itching associated with minor cuts scrapes burns

WARNINGS

For external use only

Do not use

- In eyes
- Over large areas of the body
- For more than one week unless directed by a doctor
- If you are allergic to any of the ingredients
- On deep puncture wounds, animal bites, or serious burns

Keep out of reach of children. If swallowed, get medical help or contact a poison control center right away

Directions

Clean affected area

Apply a small amount 1-3 times daily

Children under 2: Consult doctor

Inactive ingredients

Petrolactum, Liquid Paraffin, Octadecanol, Glycerol, Stearic Acid, Purified Water, Aloe